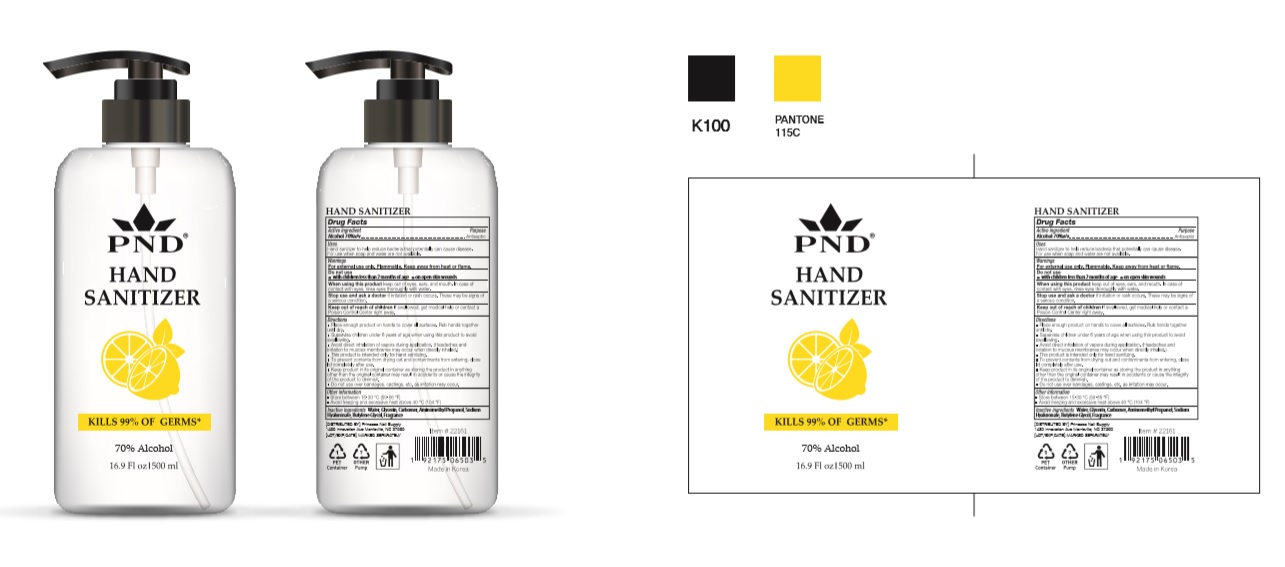 DRUG LABEL: PND HAND SANITIZER
NDC: 74339-3357 | Form: GEL
Manufacturer: PL COSMETIC
Category: otc | Type: HUMAN OTC DRUG LABEL
Date: 20200412

ACTIVE INGREDIENTS: ALCOHOL 350 mL/500 mL
INACTIVE INGREDIENTS: GLYCERIN; CARBOMER HOMOPOLYMER, UNSPECIFIED TYPE; WATER; BUTYLENE GLYCOL; HYALURONATE SODIUM; AMINOMETHYLPROPANOL

[PND HAND SANITIZER] 500 ml : 74339-3357